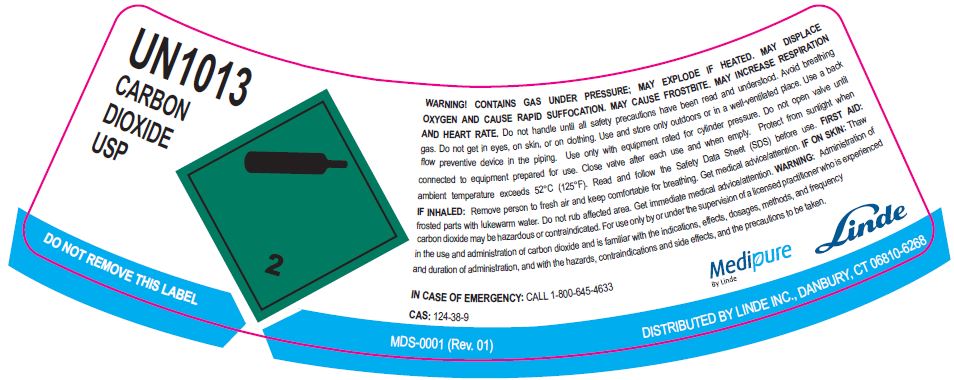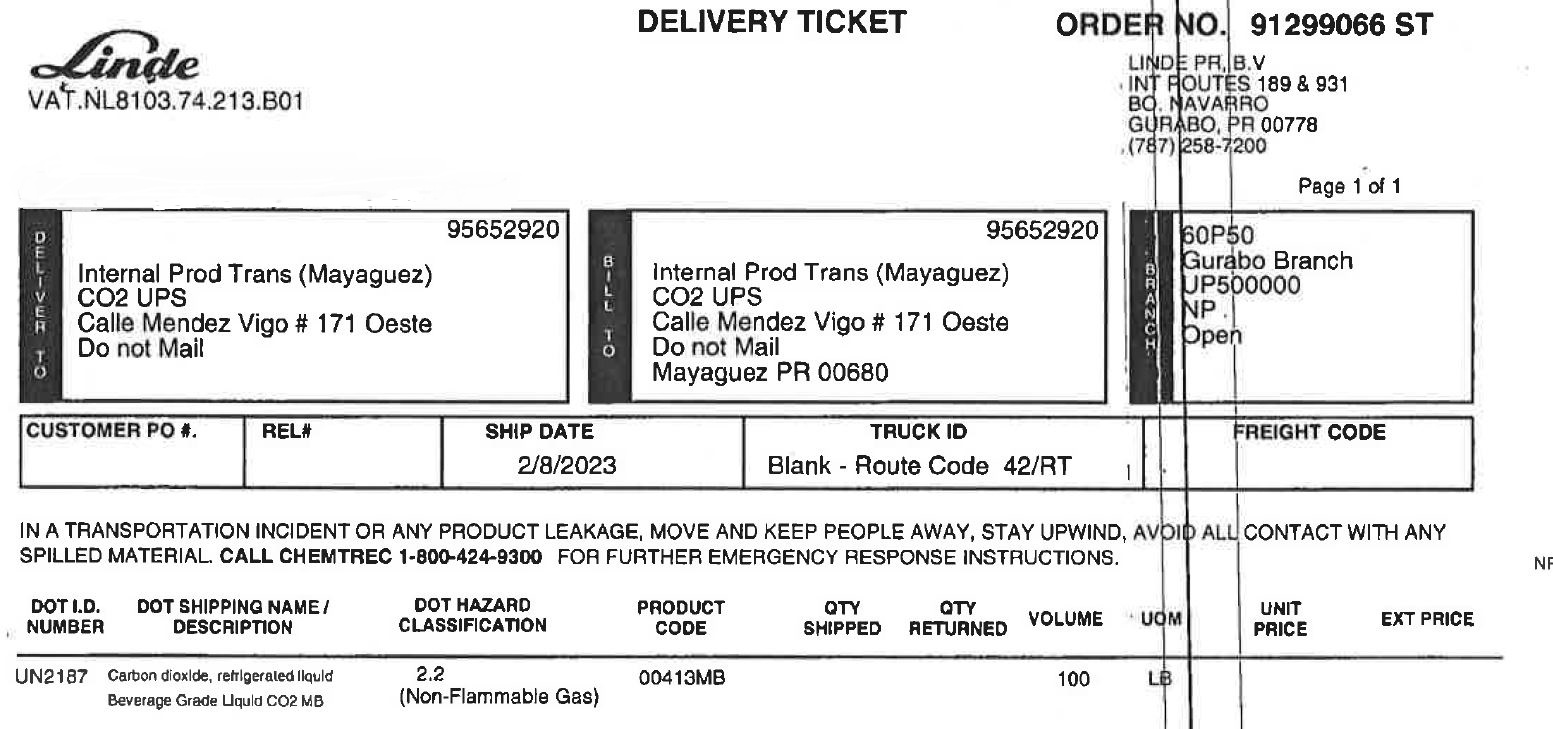 DRUG LABEL: Carbon Dioxide
NDC: 11324-003 | Form: GAS
Manufacturer: Linde Puerto Rico B.V.
Category: prescription | Type: HUMAN PRESCRIPTION DRUG LABEL
Date: 20251231

ACTIVE INGREDIENTS: CARBON DIOXIDE 990 mL/1 L

CO2 USP Gurabo